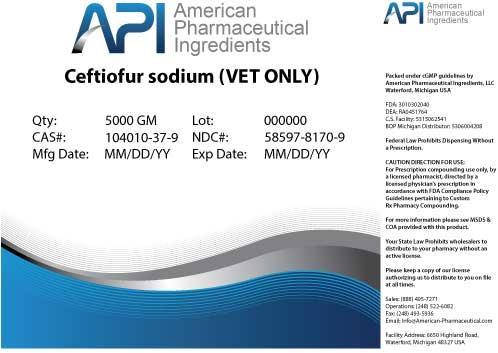 DRUG LABEL: Ceftiofur sodium
NDC: 58597-8170 | Form: POWDER
Manufacturer: AMERICAN PHARMACEUTICAL INGREDIENTS LLC
Category: other | Type: BULK INGREDIENT
Date: 20140425

ACTIVE INGREDIENTS: Ceftiofur sodium 1 g/1 g

Ceftiofur sodium